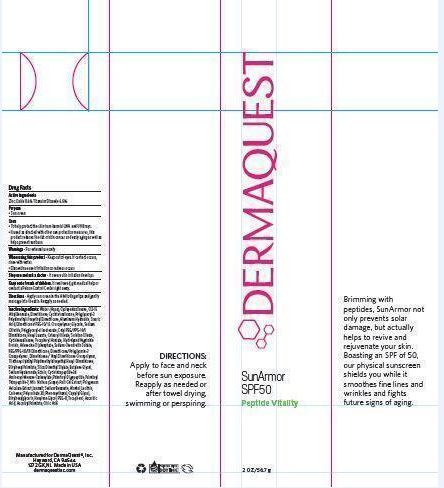 DRUG LABEL: Sun Armor SPF 50
NDC: 62742-4096 | Form: CREAM
Manufacturer: Allure Labs, Inc
Category: otc | Type: HUMAN OTC DRUG LABEL
Date: 20171129

ACTIVE INGREDIENTS: ZINC OXIDE 86 mg/1 g; TITANIUM DIOXIDE 65 mg/1 g
INACTIVE INGREDIENTS: WATER; CYCLOMETHICONE 5; ALKYL (C12-15) BENZOATE; DIMETHICONE; ALUMINUM HYDROXIDE; STEARIC ACID; GLYCERIN; SODIUM CHLORIDE; POLYGLYCERYL-4 ISOSTEARATE; CETYL PEG/PPG-10/1 DIMETHICONE (HLB 2); HEXYL LAURATE; CETEARYL OLIVATE; SORBITAN OLIVATE; CYCLOMETHICONE 6; .ALPHA.-TOCOPHEROL ACETATE; ADENOSINE TRIPHOSPHATE; SODIUM CHONDROITIN SULFATE (PORCINE; 5500 MW); PEG/PPG-18/18 DIMETHICONE; DIMETHICONE/VINYL DIMETHICONE CROSSPOLYMER (SOFT PARTICLE); ETHYLHEXYL PALMITATE; SILICA DIMETHYL SILYLATE; BUTYLENE GLYCOL; HYALURONATE SODIUM; ECTOINE; PALMITOYL TETRAPEPTIDE-7; WINE GRAPE; POLYGONUM AVICULARE TOP; ISOMALT; SODIUM BENZOATE; ALCOHOL; EGG PHOSPHOLIPIDS; CARBOMER COPOLYMER TYPE B (ALLYL PENTAERYTHRITOL CROSSLINKED); POLYSORBATE 20; PHENOXYETHANOL; CAPRYLYL GLYCOL; ETHYLHEXYLGLYCERIN; HEXYLENE GLYCOL; POLYETHYLENE GLYCOL 400; TOCOPHEROL; ASCORBIC ACID; ASCORBYL PALMITATE; CITRIC ACID MONOHYDRATE

Drug facts

ACTIVE INGREDIENT

Active Ingredients: Zinc Oxide 8.6% and Titanium Dioxide 6.5%

Purpose: Sunscreen

INDICATIONS AND USAGE

Uses: To help protect the skin from harmful UVA and UVB rays. If used as directed with other sun protection measures, this product reduces the risk of skin cancer and early aging as well as helps prevent sunburn.

Warnings: For external use only.

When using this product: Keep out of eyes. If contacts occurs, rinse with water. Discontinue use if irritation or redness occurs.

Stop use and ask a doctor: If severe skin irritation develops.

Keep out of reach of children. If swallowed, get medical help or contact a Poison Control Center right away.

DOSAGE AND ADMINISTRATION

Directions: Apply sunscreen in the AM to fingertips and gently massage into the skin. Reapply as needed.

INACTIVE INGREDIENT

Inactive Ingredients: Water (Aqua), Cyclopenatasiloxane, C12-15 Alkyl Benzoate, Dimethicone, Cyclotetrasiloxane, Polyglyceryl-3 Polydimethylsiloxyethyl Dimethicone, Alminum Hydroxide, Stearic Acid, Dimethicone/PEG-10/15 Crosspolymer, Glycerin, Sodium Chloride, Polyglyceryl-4 Isostearate, Cetyl PEG/PPG-10/1 Dimethicone, Hexyl Laurate, Cetearyl Olivate, Sorbitan Olivate, Cyclohexasiloxane, Tocopheryl Acetate, Hydrolyzed Vegetable Protein, Adenosine Triphosphate, Sodium Chondroitin Sulfate, PEG/PPG-18/18 Dimethicone, Dimethicone/Polyglycerin-3 Crosspolymer, Dimethicone / Vinyl Dimethicone Crosspolymer Triethoxysilylethyl Polydimethylsiloxyethyl Hexyl Dimethicone, Ethylhexyl Palmitate, Silica Dimethyl Silylate, Butylene Glycol, Sodium Hyaluronate, Ectoin, Cyclotetrapeptide-24 Aminocyclohexane Carboxylate, Palmitoyl Oligopepetide, Palmitoyl Tetrapeptide-7, Vitis Vinifera (Grape) Fruit Cell Extract,Polygonum Aviculare Extract, Isomalt, Sodium Benzoate, Alcohol, Lecithin, Carbomer, Polysorbate 20, Phenoxyethanol, Caprylyl Glycol, Ethylhexylglycerin, Hexylene Glycol, PEG-8, Tocopherol, Ascorbic Acid, Ascorbyl Palmitate, Citric Acid.

PACKAGE LABEL

Mnaufacture for Dermaquest Inc

Hayward, CA 94544

1272 GK, NL Made In USA